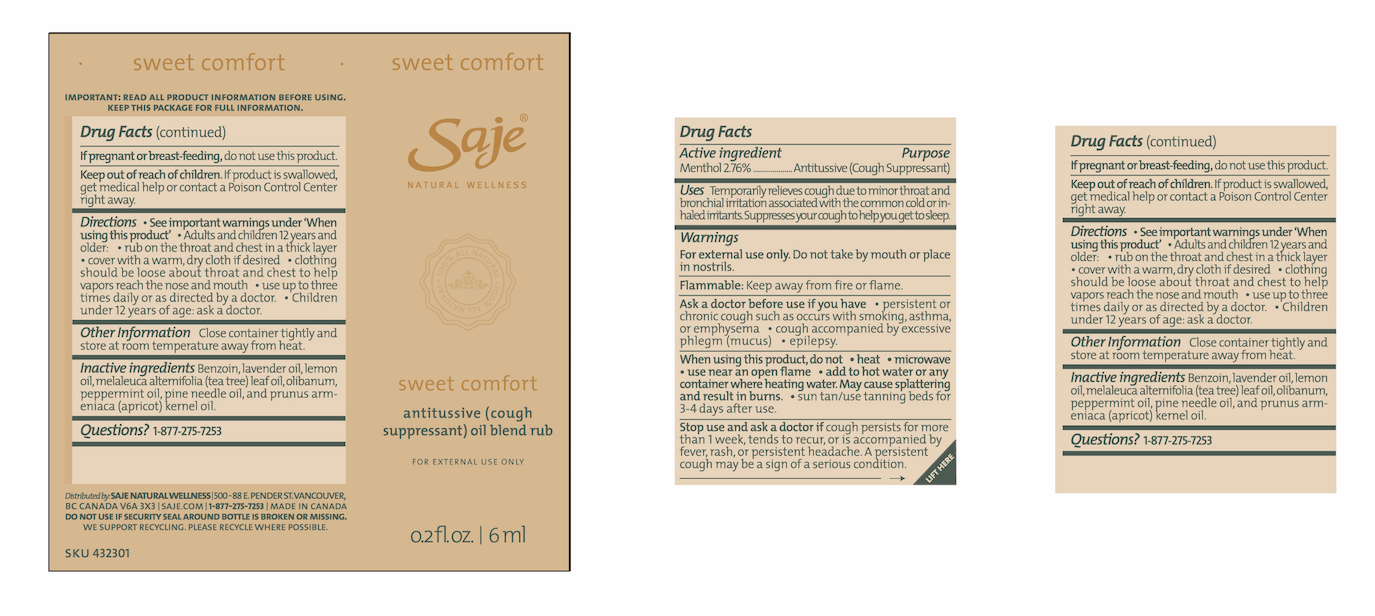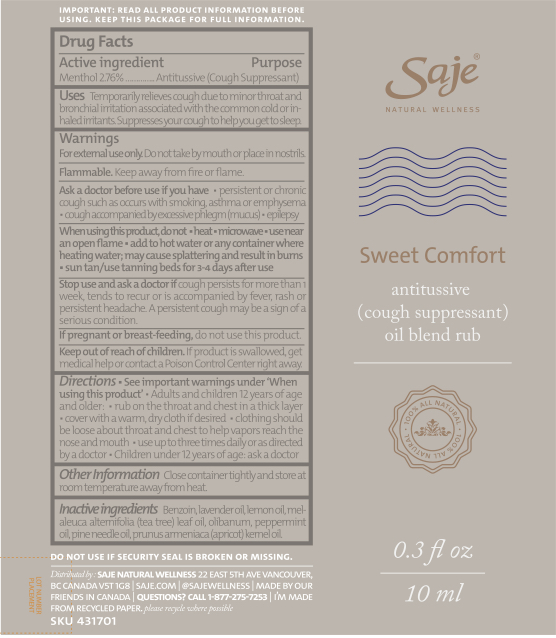 DRUG LABEL: Sweet Comfort
NDC: 70983-003 | Form: OIL
Manufacturer: Saje Natural Business Inc.
Category: otc | Type: HUMAN OTC DRUG LABEL
Date: 20260113

ACTIVE INGREDIENTS: MENTHOL 24.56 mg/1 mL
INACTIVE INGREDIENTS: STYRAX BENZOIN RESIN; LAVENDER OIL; LEMON OIL; TEA TREE OIL; FRANKINCENSE OIL; PINE NEEDLE OIL (PINUS SYLVESTRIS); APRICOT KERNEL OIL

Sweet Comfort Antitussive (Cough Suppressant) Oil Blend Rub (10 ml, 6 ml)

IMPORTANT: READ ALL PRODUCT INFORMATION BEFORE USING. KEEP THIS PACKAGE FOR FULL INFORMATION.

DRUG FACTS Active ingredient

Menthol 2.76%

Purpose Antitussive (Cough Suppressant)

Uses Temporarily relieves cough due to minor throat and bronchial irritation associated with the common cold or inhaled irritants. Supresses your cough to help you get to sleep.

Warnings

For external use only.

Do not take by mouth or place in nostrils

Flammable: Keep away from fire or flame.

Ask a doctor before use if you have

- persistent or chronic cough such as occurs with smoking, asthma, or emphysema
- cough accompanied by excessive phlegm (mucus).
- epilepsy

When using this product, do not

- heat
- microwave
- use near an open flame
- add to hot water or any container where heating water. May cause splattering and result in burns.
- sun tan/use tanning beds for 3-4 days after use.

Stop use and ask a doctor if

cough persists for more than 1 week, tends to recur, or is accompanied by fever, rash, or persistent headache. A persistent cough may be a sign of a serious condition.

If pregnant or breast-feeding,

do not use this product.

Keep out of reach of children.

If product is swallowed, get medical help or contact a Poison Control Center right away.

Directions

- See important warnings under 'When using this product'.
- Adults and children 12 years of age and older: rub on the throat and chest in a thick layer
- cover with a warm, dry cloth if desired
- clothing should be loose about throat and chest to help vapors reach the nose and mouth

DOSAGE AND ADMINISTRATION

- use up to three times daily or as directed by a doctor.
- Children under 12 years of age: ask a doctor.

Other information

- Close container tightly and store at room temperature away from heat.

Inactive ingredients

Benzoin, lavender oil, lemon oil, melaleuca alternifolia (tea tree) leaf oil, olibanum, pine needle oil, and prunus armeniaca (apricot) kernel oil.

Questions?

1-877-275-7253

Distributed by: SAJE NATURAL WELLNESS 22 East 5th Ave Vancouver, BC Canada V5T 1G8 | saje.com | 1-877-275-7253 | Made in Canada

Do not use if security seal around bottle is broken or missing.

Sweet Comfort 10 ml

SKU 431701

Sweet Comfort 6 ml

Lift Here

SKU 432301

DISPOSAL AND WASTE HANDLING

We support recycling. Please recycle where possible.

Sweet Comfort Antitussive (Cough Suppressant) Oil Blend Rub - 10 ml

sweet comfort

Saje® Natural Wellness

Sweet Comfort

Antitussive (Cough Suppressant) Oil Blend Rub

For external use only.

0.34 fl. oz. | 10 ml

Sweet Comfort Antitussive (Cough Suppressant) Oil Blend Rub - 6 ml

sweet comfort

Saje® Natural Wellness

Sweet Comfort

Antitussive (Cough Suppressant) Oil Blend Rub

For external use only.

0.2 fl. oz. | 6 ml